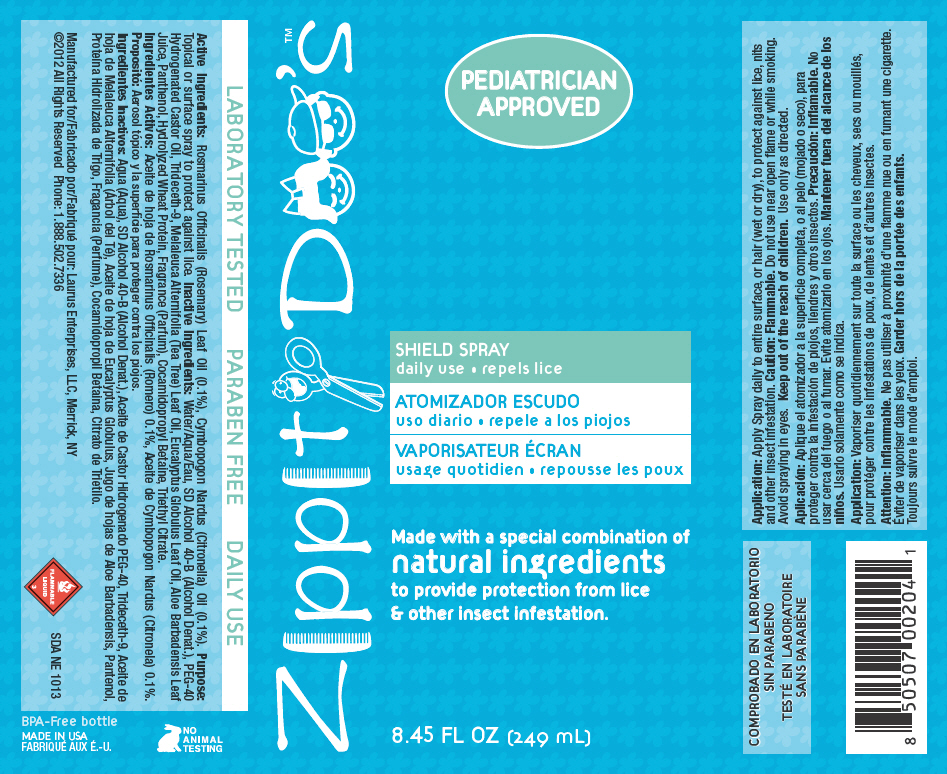 DRUG LABEL: Zippity Doos 
NDC: 57240-2041 | Form: LIQUID
Manufacturer: Laurus Enterprises, LLC
Category: homeopathic | Type: HUMAN OTC DRUG LABEL
Date: 20130304

ACTIVE INGREDIENTS: Rosemary 2.49 mg/1 mL
INACTIVE INGREDIENTS: Water; Hydrogenated Castor Oil; Tea Tree Oil; Citronella Oil; Eucalyptus Oil; Hamamelis Virginiana Top Water; Aloe Vera Leaf; Panthenol; Oxybenzone; Cocamidopropyl Betaine; Triethyl Citrate; PEG/PPG-17/18 Dimethicone

Zippity Doo's™
SHIELD SPRAY

Active Ingredients

Rosmarinus Officinalis (Rosemary) Leaf Oil (0.1%), Cymbopogon Nardus (Citronella) Oil (0.1%).

Purpose

Topical or surface spray to protect against lice.

Inactive Ingredients

Water/Aqua/Eau, SD Alcohol 40-B (Alcohol Denat.), PEG-40 Hydrogenated Castor Oil, Trideceth-9, Melaleuca Alternifolia (Tea Tree) Leaf Oil, Eucalyptus Globulus Leaf Oil, Aloe Barbadensis Leaf Juice, Panthenol, Hydrolyzed Wheat Protein, Fragrance (Parfum), Cocamidopropyl Betaine, Triethyl Citrate.

Application

INDICATIONS AND USAGE

Apply Spray daily to entire surface, or hair (wet or dry), to protect against lice, nits and other insect infestation.

Caution

Flammable.

Do not use near open flame or while smoking. Avoid spraying in eyes.

Keep out of the reach of children.

WHEN USING

Use only as directed.

PRINCIPAL DISPLAY PANEL - 249 mL Bottle Label

Zippity Doo's™

PEDIATRICIAN
APPROVED

SHIELD SPRAY
daily use • repels lice

Made with a special combination of
natural ingredients
to provide protection from lice
& other insect infestation.

8.45 FL OZ (249 mL)